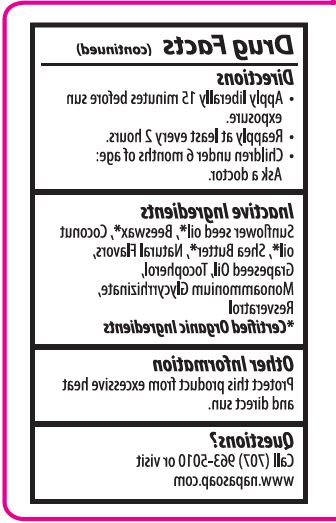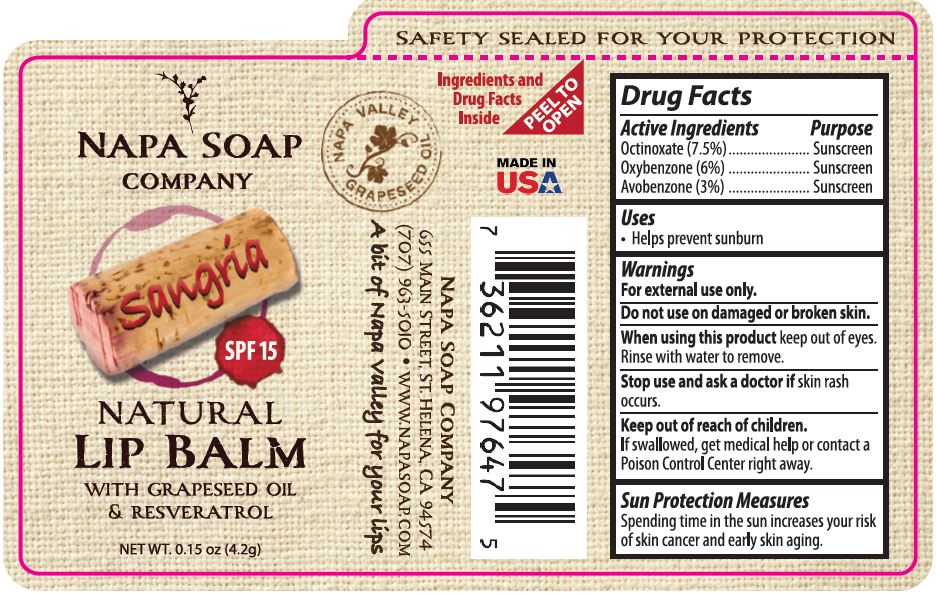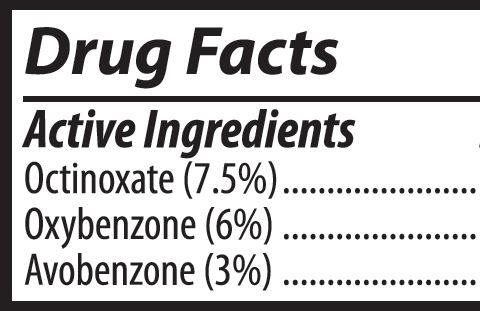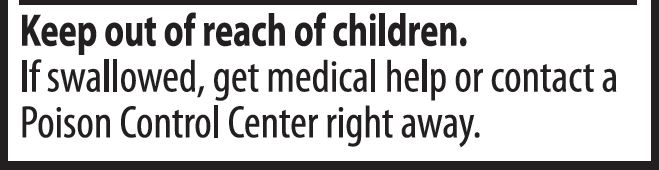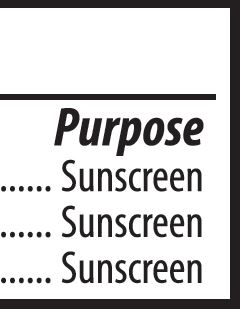 DRUG LABEL: LIP BALM
NDC: 62932-237 | Form: STICK
Manufacturer: Private Label Select Ltd CO
Category: otc | Type: HUMAN OTC DRUG LABEL
Date: 20201230

ACTIVE INGREDIENTS: OXYBENZONE 6 g/100 g; OCTINOXATE 7.5 g/100 g; AVOBENZONE 3 g/100 g
INACTIVE INGREDIENTS: SUNFLOWER OIL; WHITE WAX; GRAPE SEED OIL; COCONUT OIL; SHEA BUTTER; .BETA.-TOCOPHEROL; .DELTA.-TOCOPHEROL; AMMONIUM GLYCYRRHIZATE; .GAMMA.-TOCOPHEROL; .ALPHA.-TOCOPHEROL, D-; RESVERATROL

Napa Soap Sangria SPF 15 Natural Lip Balm